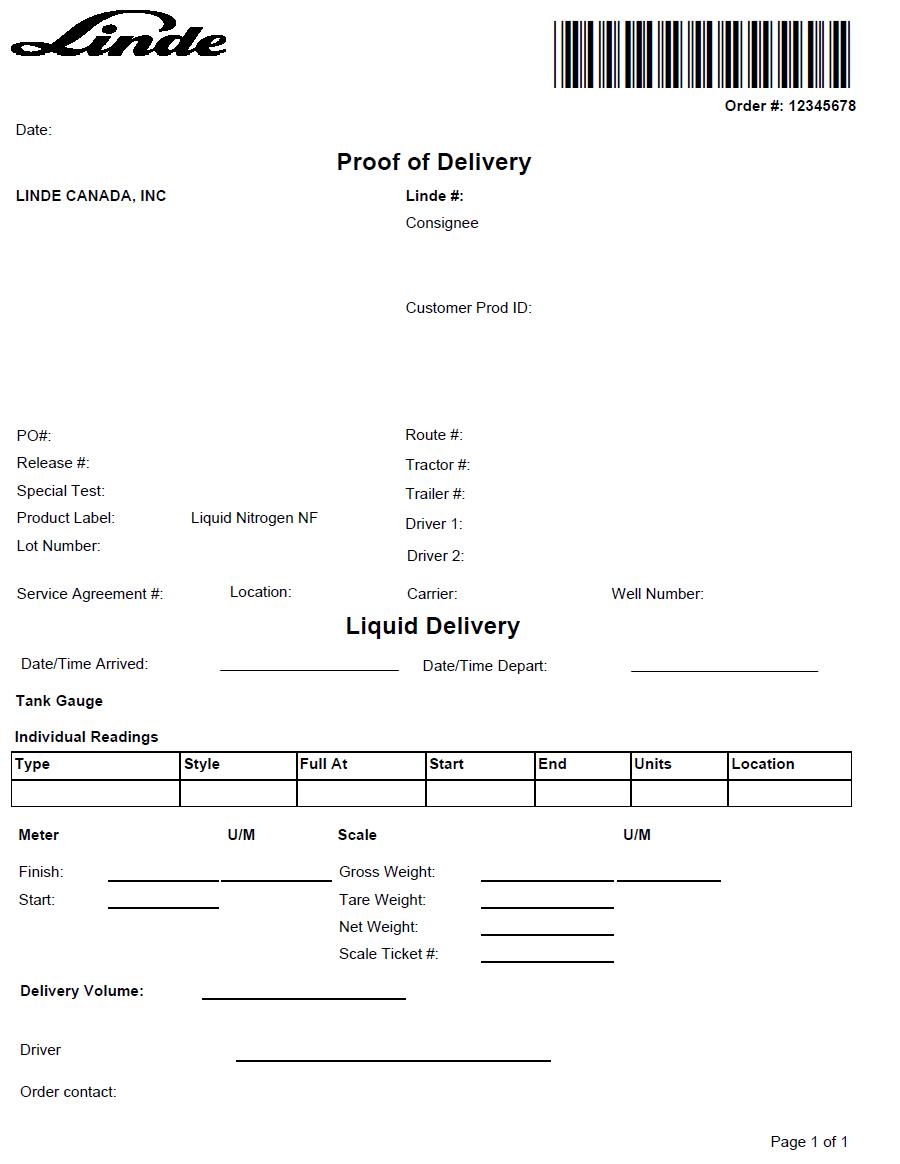 DRUG LABEL: Nitrogen
NDC: 49479-500 | Form: GAS
Manufacturer: Linde Canada Inc.
Category: prescription | Type: HUMAN PRESCRIPTION DRUG LABEL
Date: 20251230

ACTIVE INGREDIENTS: NITROGEN 990 mL/1 L

Liquid Nitrogen NF Canada